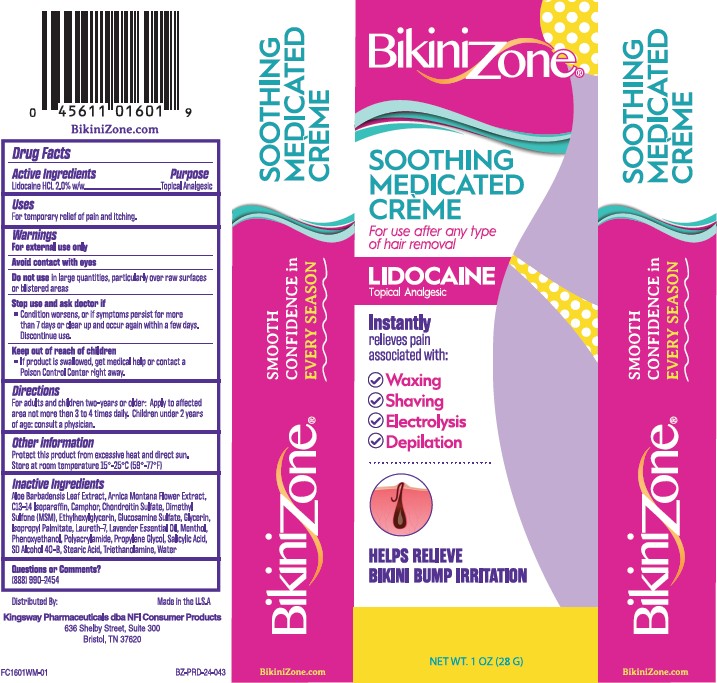 DRUG LABEL: Bikini Zone Medicated Creme
NDC: 69993-043 | Form: CREAM
Manufacturer: Kingsway Pharmaceuticals dba NFI, LLC
Category: otc | Type: HUMAN OTC DRUG LABEL
Date: 20250829

ACTIVE INGREDIENTS: LIDOCAINE 2 g/100 g
INACTIVE INGREDIENTS: ALOE VERA LEAF; ARNICA MONTANA FLOWER; C13-14 ISOPARAFFIN; CAMPHOR (NATURAL); DIMETHYL SULFONE; ETHYLHEXYLGLYCERIN; GLUCOSAMINE SULFATE; GLYCERIN; ISOPROPYL PALMITATE; LAURETH-7; LAVENDER OIL; MENTHOL, UNSPECIFIED FORM; PHENOXYETHANOL; PROPYLENE GLYCOL; SALICYLIC ACID; ALCOHOL; STEARIC ACID; TROLAMINE; WATER

Bikini Zone® Medicated Crème

Active Ingredients

Lidocaine HCL 2.0% w/w

Purpose

Topical Analgesic

Uses

For temporary relief of pain and itching.

Warnings

For external use only

Avoid contact with eyes

Do not use

in large quantities, particularly over raw surfaces or blistered areas

Stop use and ask a doctor if

- Condition worsens, or if symptoms persist for more than 7 days or clear up and occur again within a few days. Discontinue use.

Keep out of reach of children

- If product is swallowed, get medical help or contact a Poison Control Center right away.

Directions

For adults and children two-years or older: Apply to affected area not more then 3 to 4 times daily. Children under 2 years of age: consult a physician.

Other information

Protect this product from excessive heat and direct sun. Store at room temperature 15°-25°C (59°-77°F)

Inactive Ingredients

Aloe Barbadensis Leaf Extract, Arnica Montana Flower Extract, C13-14 Isoparaffin, Camphor, Chondroitin Sulfate, Dimethyl Sulfone (MSM), Ethylhexylglycerin, Glucosamine Sulfate, Glycerin, Isopropyl Palmitate, Laureth-7, Lavender Essential Oil, Menthol, Phenoxyethanol, Polyacrylamide, Propylene Glycol, Salicylic Acid, SD Alcohol 40-B, Stearic Acid, Triethanolamine, Water

Questions or Comments?

(888) 990-2454

Package/Label Principal Display Panel – Carton Label

Bikini Zone®
SOOTHING
MEDICATED
CRÈME
For use after any type
of hair removal
LIDOCAINE
Topical Analgesic
Instantly
relieves pain
associated with:

✓ Waxing
✓ Shaving
✓ Electrolysis
✓ Depilation

HELPS RELIEVE
BIKINI BUMP IRRITATION
NET WT. 1 OZ (28 G)
Distributed By:
Kingsway Pharmaceuticals dba NFI Consumer Products
636 Shelby Street, Suite 300
Bristol, TN 37620
Made in the U.S.A